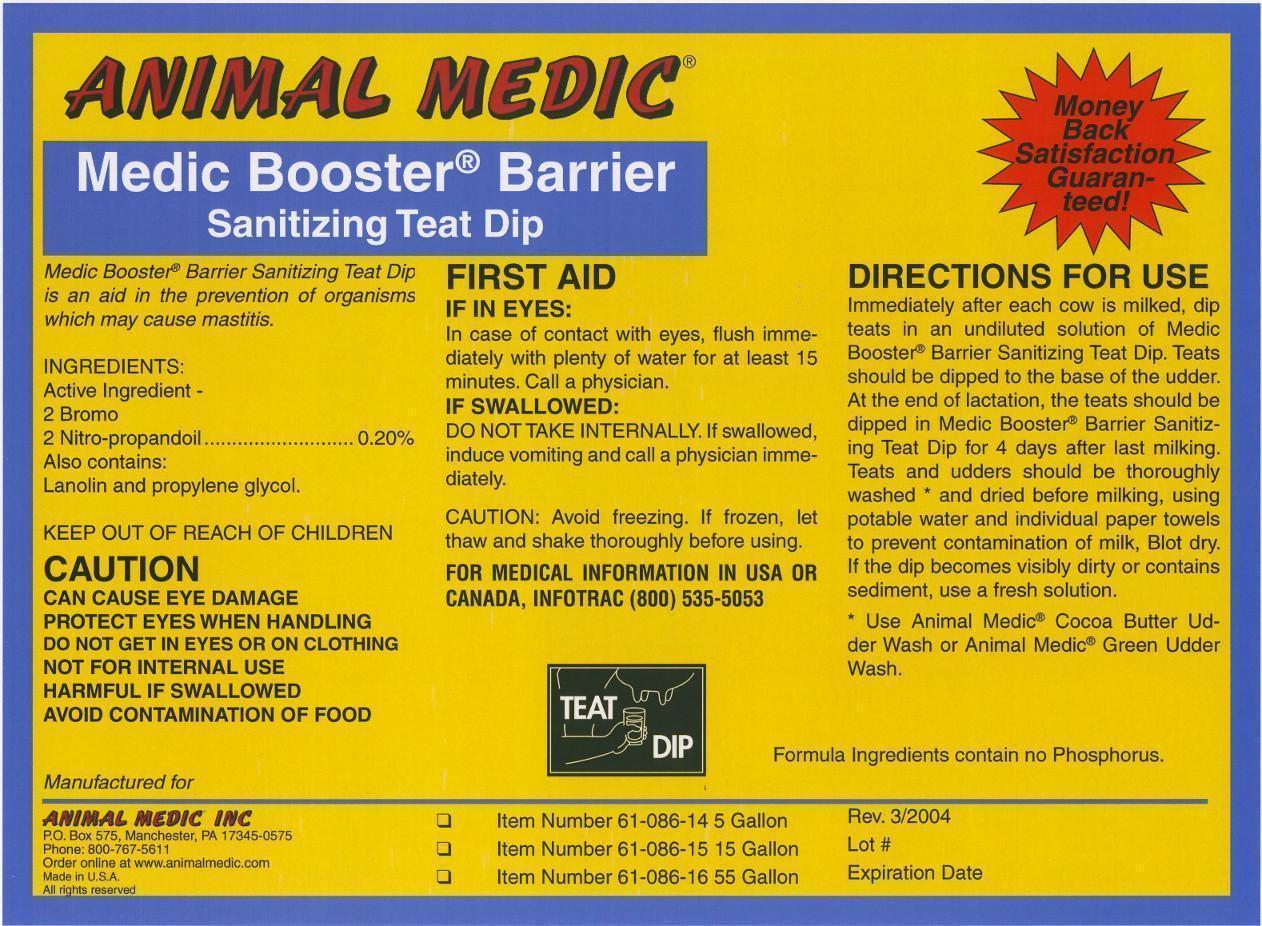 DRUG LABEL: Medic Booster Barrier
NDC: 12994-003 | Form: LIQUID
Manufacturer: Animal Medic Incorporated
Category: animal | Type: OTC ANIMAL DRUG LABEL
Date: 20130201

ACTIVE INGREDIENTS: BRONOPOL 2000 mg/1 L

Medic Booster Barrier

USER SAFETY WARNINGS

ANIMAL MEDIC
Medic Booster® Barrier
Sanitizing Teat Dip

Medic Booster® Barrier Sanitizing Teat Dip is an aid in the prevention of organisms which may cause mastitis.

INGREDIENTS:
Active Ingredient -
2 Bromo
2 Nitro-propandoil ................................................................. 0.20%
Also contains:
Lanolin and proplylene glycol.

KEEP OUT OF REACH OF CHILDREN

CAUTION
CAN CAUSE EYE DAMAGE
PROTECT EYES WHEN HANDLING
DO NOT GET IN EYES OR ON CLOTHING
NOT FOR INTERNAL USE
HARMFUL IF SWALLOWED
AVOID CONTAMINATION OF FOOD

FIRST AID

IF IN EYES:
In case of contact with eyes, flush immediatley with plenty of water for at least 15 minutes.
Call a physician.

IF SWALLOWED:
DO NOT TAKE INTERNALLY. If swallowed, induce vomiting and call a physician immediately.

CAUTION: Avoid freezing. If frozen, let thaw and shake thoroughly before using.

FOR MEDICAL INFORMATION IN USA OR CANADA, INFOTRAC (800) 535-5053.

DOSAGE AND ADMINISTRATION

DIRECTIONS FOR USE

Immediately after each cow is milked, dip teats in an undiluted solution of Medic Booster® Barrier Sanitizing Teat Dip. Teats should be dipped to the base of the udder.
At the end of lactation, the teats should be dipped in Medic Booster® Barrier Sanitizing Teat Dip for 4 days after last milking.
Teats and udders should be thoroughly washed* and dried before milking, using potable water and individual towels to prevent contamination of milk, Blot dry.
If the dip becomes visibly dirty or contains sediment, use a fresh solution.

Formula Ingredients contain no Phosphorus.

* Use Animal Medic Cocoas Butter Udder Wash or Animal Medic Green Udder Wash.